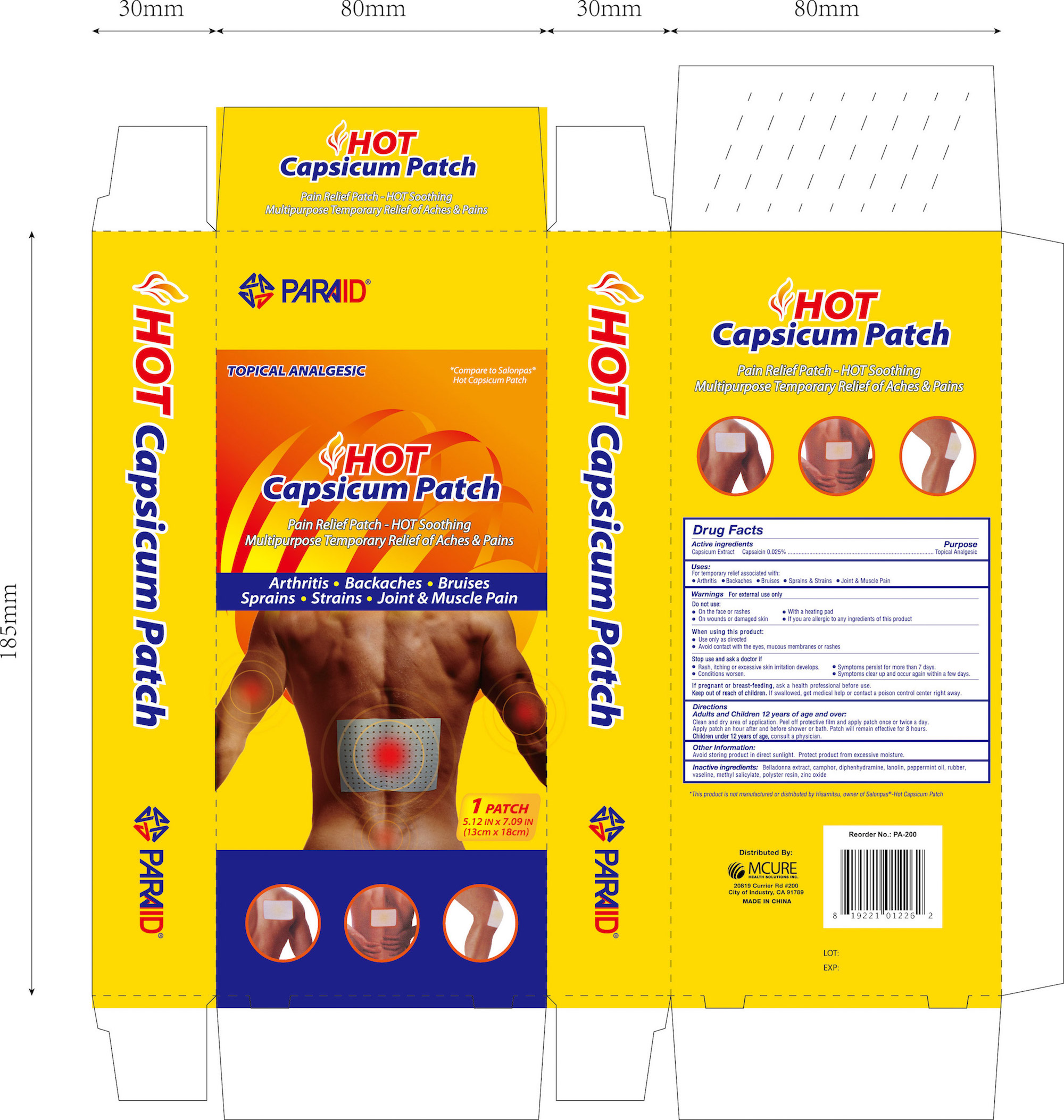 DRUG LABEL: HOT PAIN RELIEF
NDC: 71183-002 | Form: PATCH
Manufacturer: Suzhou Vastech Medical Technology Co., Ltd
Category: otc | Type: HUMAN OTC DRUG LABEL
Date: 20170628

ACTIVE INGREDIENTS: CAPSAICIN 1.2 mg/1000 mg
INACTIVE INGREDIENTS: BELLADONNA LEAF; CAMPHOR (SYNTHETIC); DIPHENHYDRAMINE; PEPPERMINT OIL; NATURAL LATEX RUBBER; LANOLIN; METHYL SALICYLATE; ZINC OXIDE; LIQUID PETROLEUM

Active ingredients Purpose

Capsicum Extract Capsaicin 0.025%..............................Topical Analgesic

Uses

For temporary relief associated with:

- Arthritis
- Backaches
- Bruises
- Sprains & Strains
- Joint & Muscle Pain

Warnings

For external use only

Do not use:

- On the face or rashes
- With a heating pad
- On wounds or damaged skin
- if you are allergic to any ingredients of this product

When using this product:

- Use only as directed
- Avoid contact with the eyes, mucous membranes or rashes

Stop use and ask a doctor if:

- Rash, itching or excessive skin irritation develops
- Conditions worsen
- Symptoms persist for more than 7 days
- Symptoms clear up and occur again within a few days

PREGNANCY OR BREAST FEEDING

If pregnant or breast-feeding, ask a health professional before use.

Keep out of reach of children.

If swallowed, get medical help or contact a Poision Control Center right away.

Directions

Adults and Children 12 years of age and over:

Clean and dry affected area.
Peel off protective film and apply patch once or twice a day.
Apply patch an hour after and before shower or bath. Patch will remain effective for 8 hours.

Children Under 12 Years of Age: Consult a physician.

Inactive ingredients

Belladonna extract, camphor, diphenhydramine, lanolin, peppermint oil, rubber, vaseline, methyl salicylate, polyster resin, zinc oxide

DOSAGE AND ADMINISTRATION

Distributed by:

MCURE HEALTH SOLUTIONS INC.

20819 Currier Rd #200

City of Industry, CA 91789

MADE IN CHINA